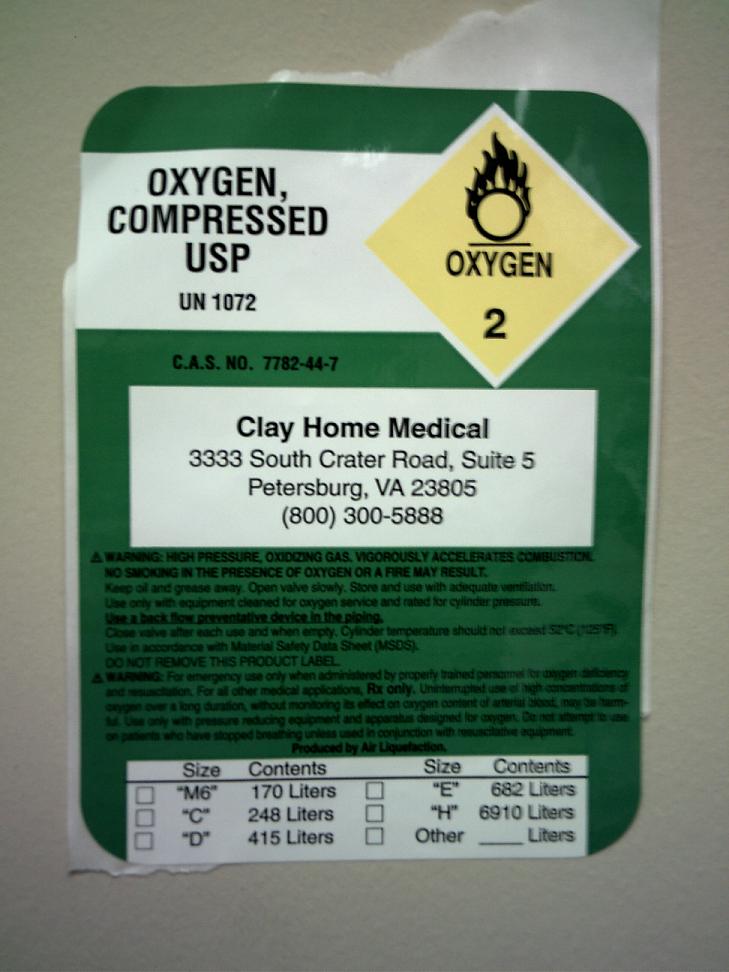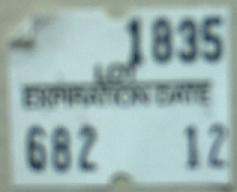 DRUG LABEL: Oxygen
NDC: 63293-0001 | Form: GAS
Manufacturer: Clay Home Medical
Category: prescription | Type: HUMAN PRESCRIPTION DRUG LABEL
Date: 20100106

ACTIVE INGREDIENTS: Oxygen 99 L/100 L

Oxygen